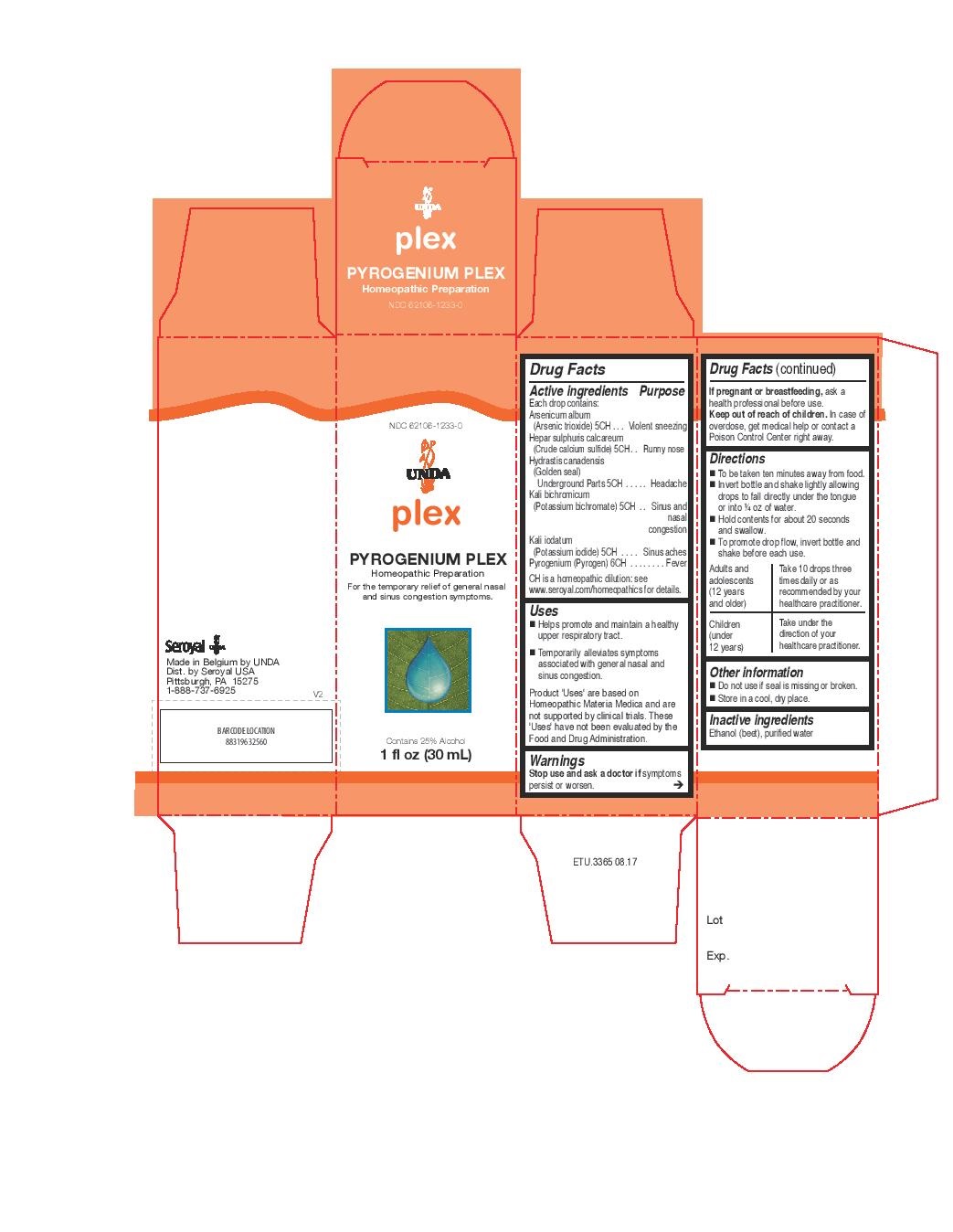 DRUG LABEL: PYROGENIUM PLEX
NDC: 62106-1233 | Form: LIQUID
Manufacturer: Seroyal USA
Category: homeopathic | Type: HUMAN OTC DRUG LABEL
Date: 20221109

ACTIVE INGREDIENTS: CALCIUM SULFIDE 5 [hp_C]/30 mL; GOLDENSEAL 5 [hp_C]/30 mL; POTASSIUM DICHROMATE 5 [hp_C]/30 mL; ARSENIC TRIOXIDE 5 [hp_C]/30 mL; POTASSIUM IODIDE 5 [hp_C]/30 mL; RANCID BEEF 6 [hp_C]/30 mL
INACTIVE INGREDIENTS: WATER; ALCOHOL

PYROGENIUM PLEX

Active ingredients

Each drop contains:

Arsenicum album (Arsenic trioxide) 5CH
Hepar sulphuris calcareum (Crude calcium sulfide) 5CH
Hydrastis canadensis (Golden seal) Underground Parts 5CH
Kali bichromicum (Potassium bichromate) 5CH
Kali iodatum (Potassium iodide) 5CH
Pyrogenium (Pyrogen) 6CH

Uses
Helps promote and maintain a healthy upper respiratory tract.
Temporarily alleviates symptoms associated with general nasal and sinus congestion.

Warnings
Stop use and ask a doctor if symptoms persist or worsen.

If pregnant or breastfeeding, ask a health professional before use.
Keep out of reach of children.

In case of overdose, get medical help or contact a Poison Control Center right away.

Stop use and ask a doctor if symptoms persist or worsen.

PREGNANCY OR BREAST FEEDING

If pregnant or breastfeeding, ask a health professional before use.

Keep out of reach of children.

OVERDOSAGE

In case of overdose, get medical help or contact a Poison Control Center right away.

Inactive ingredients
Ethanol (beet), purified water

Other information
Do not use if seal is missing or broken.
Store in a cool, dry place.

Directions
To be taken ten minutes away from food.

Invert bottle and shake lightly allowing drops to fall directly under the tongue or into ¼ oz of water.
Hold contents for about 20 seconds and swallow.

To promote drop flow, invert bottle and shake before each use.

Adults and adolescents (12 years and older)

Take 10 drops three times daily or as recommended by your healthcare practitioner.

Children (under 12 years)

Take under the direction of your healthcare practitioner.

Uses
Helps promote and maintain a healthy upper respiratory tract.
Temporarily alleviates symptoms associated with general nasal and sinus congestion.

Directions
To be taken ten minutes away from food.

Invert bottle and shake lightly allowing drops to fall directly under the tongue or into ¼ oz of water.
Hold contents for about 20 seconds and swallow.

To promote drop flow, invert bottle and shake before each use.

Adults and adolescents (12 years and older)

Take 10 drops three times daily or as recommended by your healthcare practitioner.

Children (under 12 years)

Take under the direction of your healthcare practitioner.

PACKAGE LABEL

NDC 62106-1233-0

UNDA

plex

PYROGENIUM PLEX

Homeopathic Preparation

For the temporary relief of general nasal
and sinus congestion symptoms.

Contains 25% Alcohol
1 fl oz (30 mL)